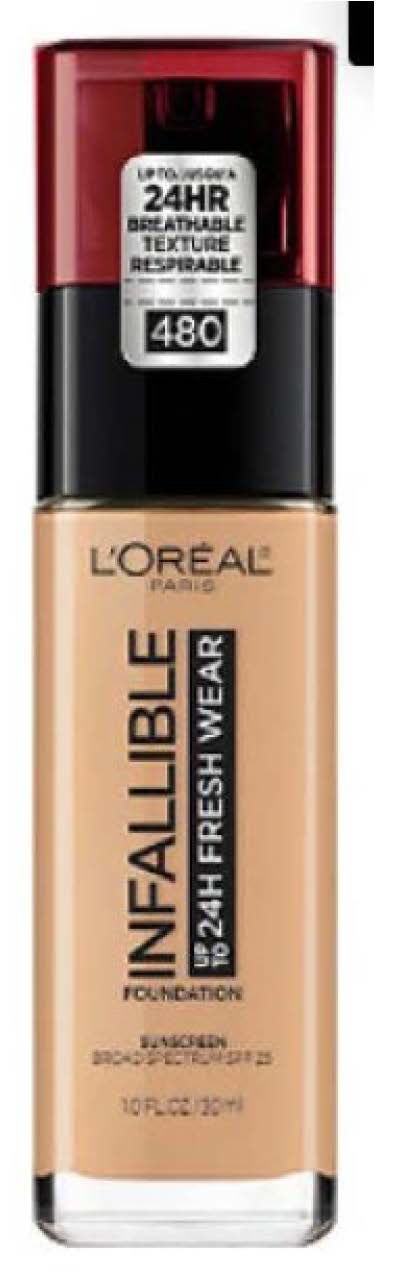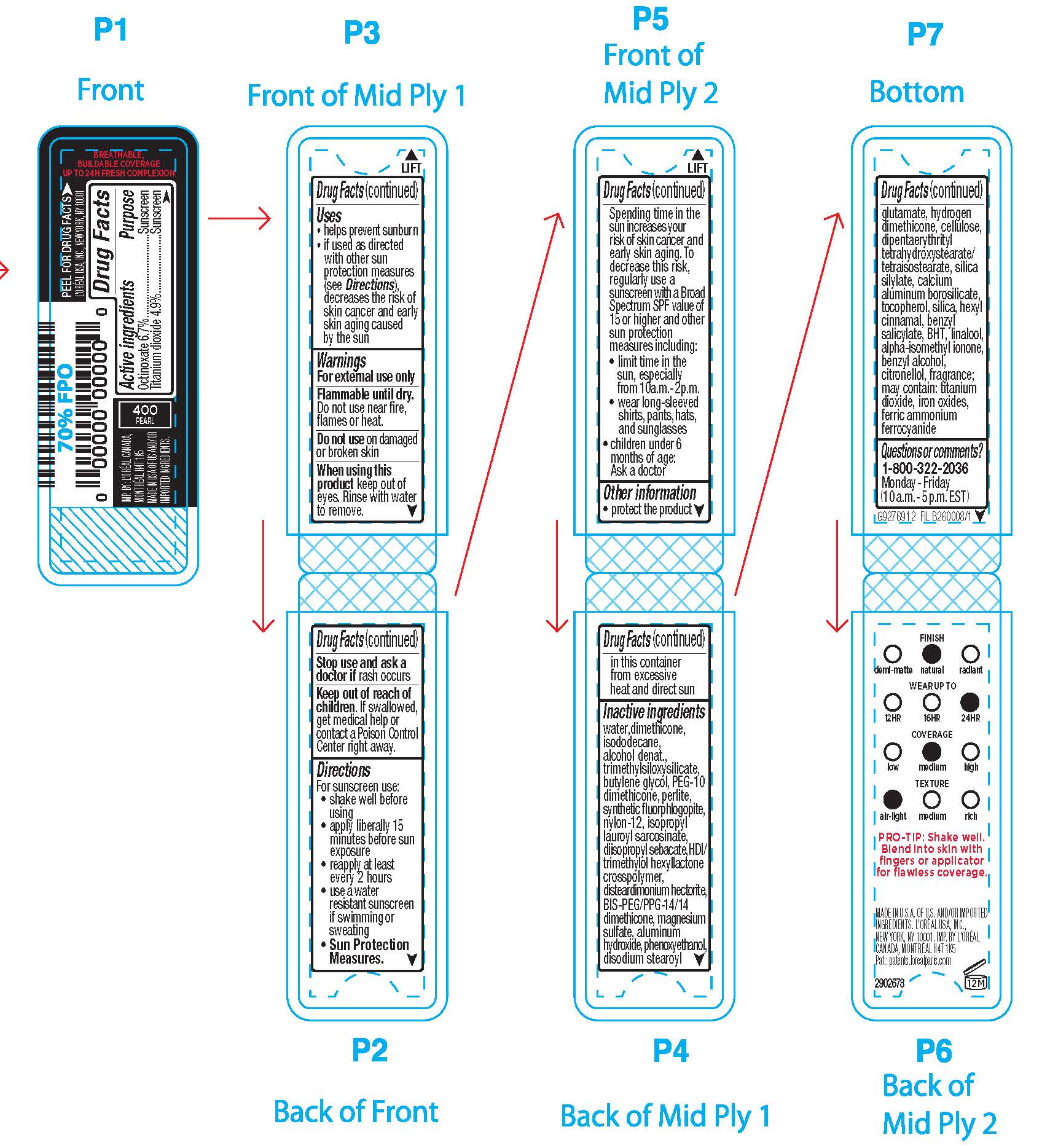 DRUG LABEL: LOreal Paris Infallible Up to 24 H Fresh Wear Foundation Broad Spectrum SPF 25 Sunscreen
NDC: 49967-009 | Form: LIQUID
Manufacturer: L'Oreal USA Products Inc
Category: otc | Type: HUMAN OTC DRUG LABEL
Date: 20231229

ACTIVE INGREDIENTS: OCTINOXATE 67 mg/1 mL; TITANIUM DIOXIDE 36 mg/1 mL
INACTIVE INGREDIENTS: WATER; DIMETHICONE; ISODODECANE; ALCOHOL; TRIMETHYLSILOXYSILICATE (M/Q 0.6-0.8); BUTYLENE GLYCOL; PEG-10 DIMETHICONE (600 CST); PERLITE; MAGNESIUM POTASSIUM ALUMINOSILICATE FLUORIDE; NYLON-12; ISOPROPYL LAUROYL SARCOSINATE; DIISOPROPYL SEBACATE; DISTEARDIMONIUM HECTORITE; HEXAMETHYLENE DIISOCYANATE/TRIMETHYLOL HEXYLLACTONE CROSSPOLYMER; BIS-PEG/PPG-14/14 DIMETHICONE; MAGNESIUM SULFATE, UNSPECIFIED FORM; ALUMINUM HYDROXIDE; PHENOXYETHANOL; DISODIUM STEAROYL GLUTAMATE; HYDROGEN DIMETHICONE (13 CST); DIPENTAERYTHRITYL TETRAHYDROXYSTEARATE/TETRAISOSTEARATE; TOCOPHEROL; .ALPHA.-HEXYLCINNAMALDEHYDE; SILICON DIOXIDE; ISOBUTANE; BENZYL SALICYLATE; LINALOOL, (+/-)-; ISOMETHYL-.ALPHA.-IONONE; BENZYL ALCOHOL; BUTYLATED HYDROXYTOLUENE; .BETA.-CITRONELLOL, (R)-; FERRIC OXIDE RED; FERRIC AMMONIUM FERROCYANIDE

Drug Facts

Active ingredients

Octinoxate 6.7%

Titanium dioxide 3.6%

Purpose

Sunscreen

Uses

- helps prevent sunburn

- if used as directed with other sun protection measures (see Directions), decreases the risk of skin cancer and early skin aging caused by the sun

Warnings

For external use only

Flammable until dry.

Do not use near fire, flame or heat.

Do not use

on damaged or broken skin

When using this product

keep out of eyes. Rinse with water to remove.

Stop use and ask a doctor if

rash occurs

Keep out of reach of children.

If swallowed, get medical help or contact a Poison Control Center right away.

Directions

For sunscreen use:

● shake well

● apply liberally 15 minutes before sun exposure

● reapply at least every 2 hours

● use a water resistant sunscreen if swimming or sweating

● Sun Protection Measures. Spending time in the sun increases your risk of skin cancer and early skin aging. To decrease this risk, regularly use a sunscreen with a Broad Spectrum SPF value of 15 or higher and other sun protection measures including:

● limit time in the sun, especially from 10 a.m. – 2 p.m.

● wear long-sleeved shirts, pants, hats, and sunglasses

● children under 6 months of age: Ask a doctor

Other information

protect the product in this container from excessive heat and direct sun

Inactive ingredients

water, dimethicone, isododecane, alcohol denat., trimethylsiloxysilicate, butylene glycol, PEG-10 dimethicone, perlite, synthetic fluorphlogopite, nylon-12, isopropyl lauroyl sarcosinate, diisopropyl sebacate, disteardimonium hectorite, HDI/trimethylol hexyllactone crosspolymer, bis-PEG/PPG-14/14 dimethicone, magnesium sulfate, aluminum hydroxide, phenoxyethanol, disodium stearoyl glutamate, hydrogen dimethicone, dipentaerythrityl tetrahydroxystearate/tetraisostearate, fragrance, silica silylate, acrylonitrile/methyl methacrylate/vinylidene chloride copolymer, tocopherol, hexyl cinnamal, silica, isobutane, benzyl salicylate, linalool, alpha-isomethyl ionone, benzyl alcohol, BHT, citronellol, may contain: titanium dioxide, iron oxides, ferric ammonium ferrocyanide

Questions or comments?

1-800-322-2036

Monday - Friday

(10 a.m. - 5 p.m. EST)